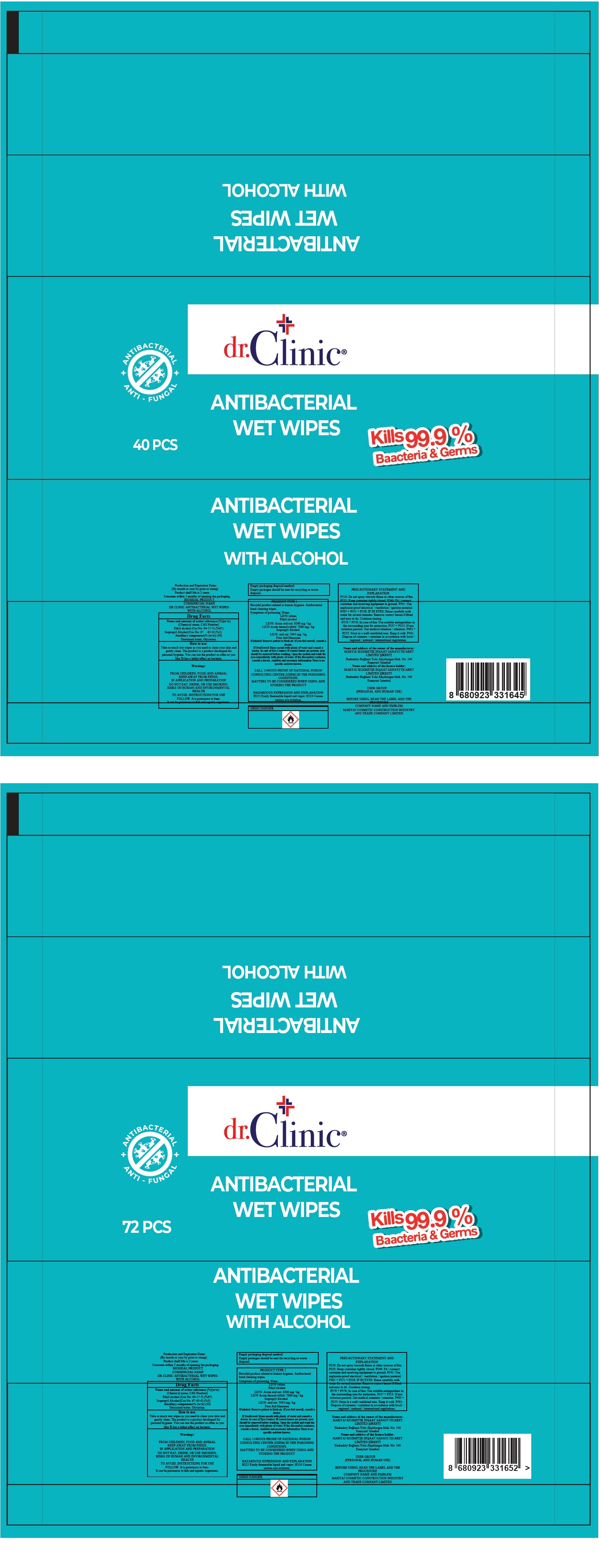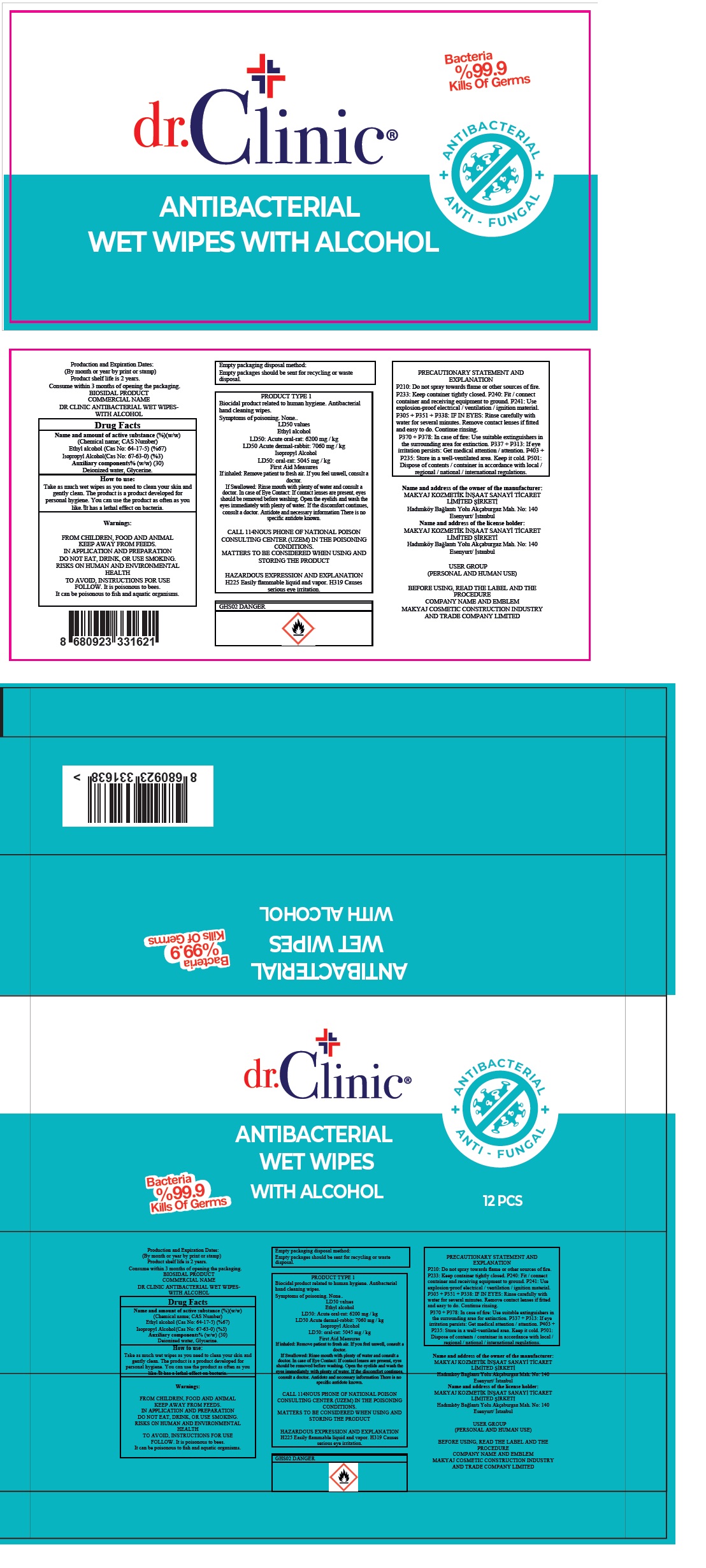 DRUG LABEL: dr.Clinic ANTIBACTERIAL WET WIPES WITH ALCOHOL
NDC: 76725-003 | Form: CLOTH
Manufacturer: MAKYAJ KOZMETIK INSAAT SANAYI VE TICARET LIMITED SIRKETI
Category: otc | Type: HUMAN OTC DRUG LABEL
Date: 20200602

ACTIVE INGREDIENTS: ALCOHOL 67 mL/100 g
INACTIVE INGREDIENTS: ISOPROPYL ALCOHOL; WATER; GLYCERIN

dr.Clinic® ANTIBACTERIAL WET WIPES WITH ALCOHOL

Name and amount of active substance (%) (w/w)

(Chemical name; CAS number)

Ethyl alcohol (Cas No: 64-17-5) (%67)

Purpose

Antibacterial

Uses:

- hand wipes to decrease bacteria on the skin
- recommended for repeated use
- for use when soap and water are not available

Warnings:

FROM CHILDREN, FOOD AND ANIMAL KEEP AWAY FROM FEEDS.
IN APPLICATION AND PREPARATION DO NOT EAT, DRINK, OR USE SMOKING.
RISKS ON HUMAN AND ENVIRONMENTAL HEALTH
TO AVOID, INSTRUCTIONS FOR USE FOLLOW. It is poisonous to bees.
It can be poisonous to fish and aquatic organisms.

Keep out of reach of children.

How to use:

Take as much wet wipes as you need to clean your skin and gently clean. The product is a product developed for personal hygiene. You can use the product as often as you like.! It has a lethal effect on bacteria.

Auxiliary components% (w/w) (30)

Isopropyl Alcohol (Cas No: 67-63-0) (%3)

Deionized water, Glycerine.

ANTI - FUNGAL

Bacteria %99.9 Kills Of Germs

Product shelf life is 2 years.
Consume within 3 months of opening the packaging.
BIOSIDAL PRODUCT

Empty packaging disposal method:
Empty packages should be sent for recycling or waste disposal.

PRODUCT TYPE 1
Biocidal product related to human hygiene. Antibacterial hand cleaning wipes.
Symptoms of poisoning. None.
LD50 values
Ethyl alcohol
LD50: Acute oral-rat: 6200 mg / kg
LD50 Acute dermal-rabbit: 7060 mg / kg
Isopropyl Alcohol
LD50: oral-rat: 5045 mg / kg
First Aid Measures
If inhaled: Remove patient to fresh air. If you feel unwell, consult a doctor.
If Swallowed: Rinse mouth with plenty of water and consult a doctor. In case of Eye Contact: If contact lenses are present, eyes should be removed before washing. Open the eyelids and wash the eyes immediately with plenty of water. If the discomfort continues, consult a doctor. Antidote and necessary information There is no specific antidote known.

CALL 114NOUS PHONE OF NATIONAL POISON CONSULTING CENTER (UZEM) IN THE POISONING CONDITIONS.
MATTERS TO BE CONSIDERED WHEN USING AND STORING THE PRODUCT

HAZARDOUS EXPRESSION AND EXPLANATION
H225 Easily flammable liquid and vapor. H319 Causes serious eye irritation.

PRECAUTIONARY STATEMENT AND EXPLANATION
P210: Do not spray towards flame or other sources of fire.
P233: Keep container tightly closed. P240: Fit / connect container and receiving equipment to ground. P241: Use explosion-proof electrical / ventilation / ignition material. P305 + P351 + P338: IF IN EYES: Rinse carefully with water for several minutes. Remove contact lenses if fitted and easy to do. Continue rinsing.
P370 + P378: In case of fire: Use suitable extinguishers in the surrounding area for extinction. P337 + P313: If eye irritation persists: Get medical attention / attention. P403 + P235: Store in a well-ventilated area. Keep it cold. P501: Dispose of contents / container in accordance with local / regional / national / international regulations.

Name and address of the owner of the manufacturer:
MAKYAJ KOZMETIK INSAAT SANAYI TICARET LIMITED SIRKETI
Hadımköy Baglantı Yolu Akçaburgaz Mah. No: 140
Esenyurt/ Istanbul
Name and address of the license holder:
MAKYAJ KOZMETIK INSAAT SANAYI TICARET LIMITED SIRKETI
Hadımköy Baglantı Yolu Akçaburgaz Mah. No: 140
Esenyurt/ Istanbul

USER GROUP
(PERSONAL AND HUMAN USE)

BEFORE USING, READ THE LABEL AND THE PROCEDURE
COMPANY NAME AND EMBLEM
MAKYAJ COSMETIC CONSTRUCTION INDUSTRY AND TRADE COMPANY LIMITED